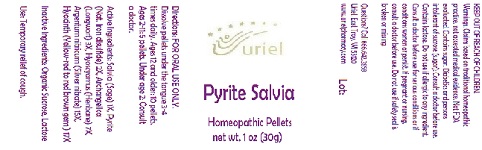 DRUG LABEL: Pyrite Salvia
NDC: 48951-8315 | Form: PELLET
Manufacturer: Uriel Pharmacy Inc
Category: homeopathic | Type: HUMAN OTC DRUG LABEL
Date: 20180606

ACTIVE INGREDIENTS: ANGELICA ARCHANGELICA ROOT 3 [hp_X]/1 1; SAGE 3 [hp_X]/1 1; HYOSCYAMUS NIGER 7 [hp_X]/1 1; SILVER NITRATE 15 [hp_X]/1 1
INACTIVE INGREDIENTS: SUCROSE; LACTOSE, UNSPECIFIED FORM

Pyrite Salvia

INDICATIONS AND USAGE

Directions: FOR ORAL USE ONLY.

DOSAGE AND ADMINISTRATION

Dissolve pellets under the tongue 3-4
times daily. Ages 12 and older: 10 pellets.
Ages 2-11: 5 pellets. Under age 2: Consult
a doctor.

ACTIVE INGREDIENT

Active Ingredients: Salvia (Sage) 1X, Pyrite (Nat. Iron disulfide) 2X, Archangelica (Longwort) 3X, Hyoscyamus (Henbane) 7X, Argentum nitricum (Silver nitrate) 15X, Hyacinth (Yellow-red to red brown gem) 17X

Inactive Ingredients: Organic Sucrose, Lactose

PURPOSE

Use: Temporary relief of cough.

KEEP OUT OF REACH OF CHILDREN.

WARNINGS

Warnings: Claims based on traditional homeopathic practice, not accepted medical evidence. Not FDA evaluated. Contains sugar. Diabetics and persons intolerant of sucrose (sugar): Consult a doctor before use. Contains lactose. Do not use if allergic to any ingredient. Consult a doctor before use for serious conditions or if conditions worsen or persist. If pregnant or nursing, consult a doctor before use. Do not use if safety seal is broken or missing.

Questions? Call 866.642.2858
Uriel, East Troy, WI 53120
www.urielpharmacy.com